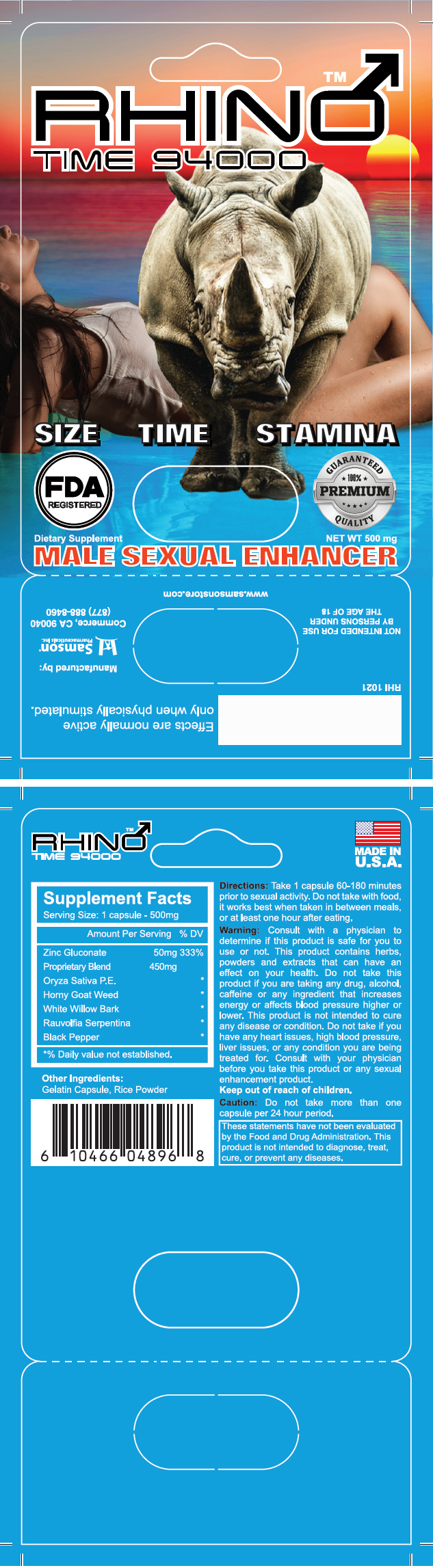 DRUG LABEL: Rhino Time 94000
NDC: 20146-1021 | Form: CAPSULE
Manufacturer: SAMSON PHARMACEUTICAL
Category: other | Type: DIETARY SUPPLEMENT
Date: 20190523

ACTIVE INGREDIENTS: Zinc Gluconate 50 mg/1 1
INACTIVE INGREDIENTS: Brown Rice; Epimedium Grandiflorum Top; Salix Alba Bark; Rauwolfia Serpentina; Black Pepper

Rhino Time 94000 Male Sexual Enhancer Pill

HEALTH CLAIM

Dietary Supplement

Net WT 500 mg

Directions

Take 1 capsule 60-180 minutes prior to sexual activity. Do not take with food, it works best when taken in between meals, or at least one hour after eating.

Warning

Consult with a physician to determine if this product is safe for you to use or not. This product contains herbs, powders and extracts that can have an effect on your health. Do not take this product if you are taking any drug, alcohol, caffeine or any ingredient that increases energy or affects blood pressure higher or lower. This product is not intended to cure any disease or condition. Do not take if you have any heart issues, high blood pressure, liver issues, or any condition you are being treated for. Consult with your physician before you take this product or any sexual enhancement product. Keep out of reach of children.

Caution

Do not take more than one capsule per 24 hour period.

STATEMENT OF IDENTITY

Supplement Facts
Serving Size: 1 capsule - 500mg
Amount Per Serving |  | % DV
Zinc Gluconate | 50mg | 333%
Proprietary Blend | 450mg
Oryza Sativa P.E. |  | [% Daily value not established.]
Horny Goat Weed
White Willow Bark
Rauvolfia Serpentina
Black Pepper

Other Ingredients:
Gelatin Capsule, Rice Powder

HEALTH CLAIM

Effects are normally active only when physically stimulated.

These statements have not been evaluated by the Food and Drug Administration. This product is not intended to diagnose, treat, cure, or prevent any diseases.

NOT INTENDED FOR USE BY PERSONS UNDER THE AGE OF 18

PRINCIPAL DISPLAY PANEL - 500 mg Capsule Blister Pack

RHINO™
TIME 94000

SIZE
TIME
STAMINA

FDA
REGISTERED

GUARANTEED
100% PREMIUM
QUALITY

Dietary Supplement
NET WT 500 mg

MALE SEXUAL ENHANCER